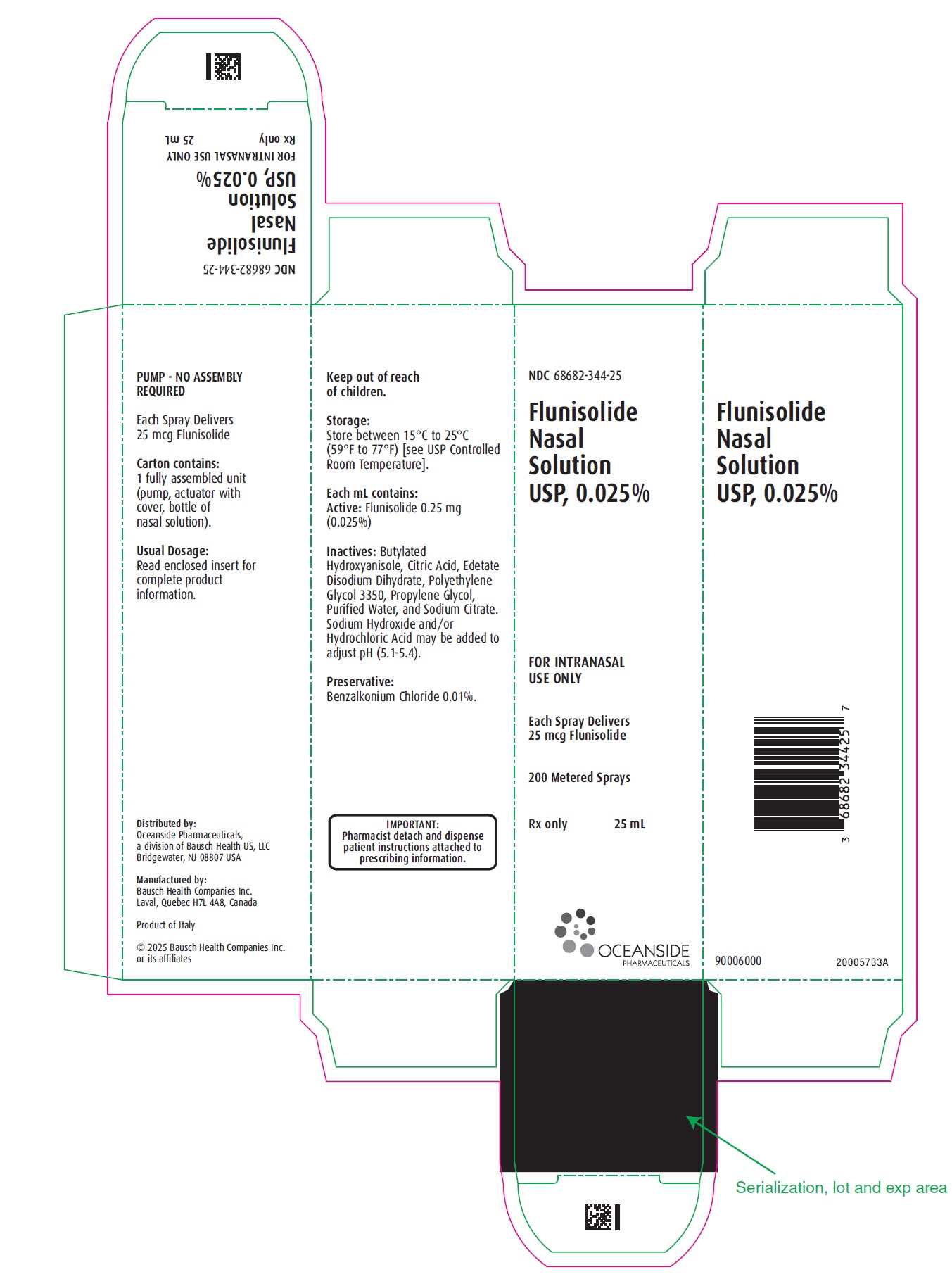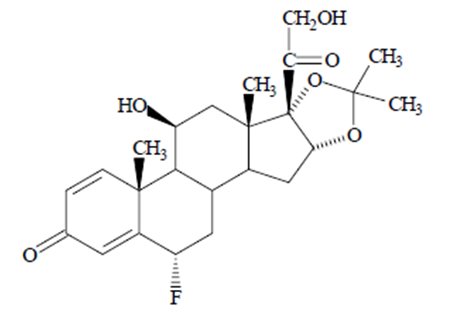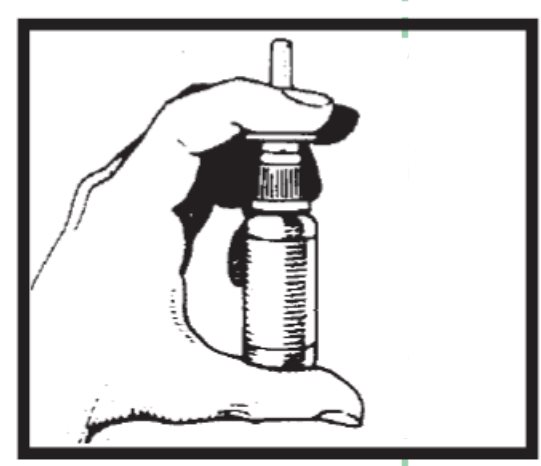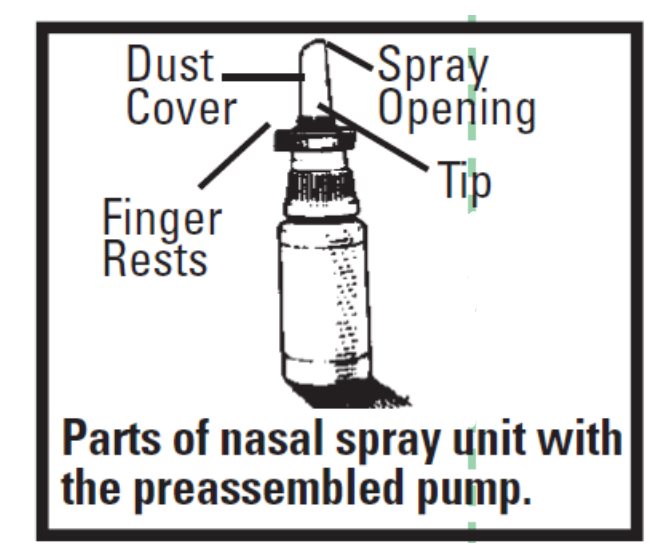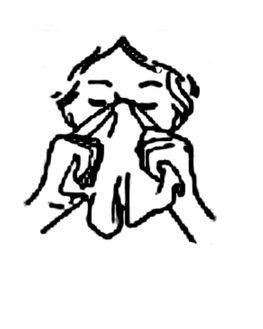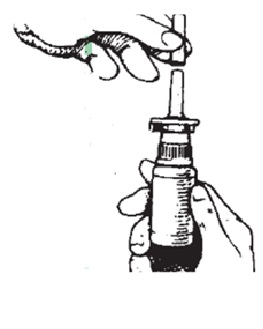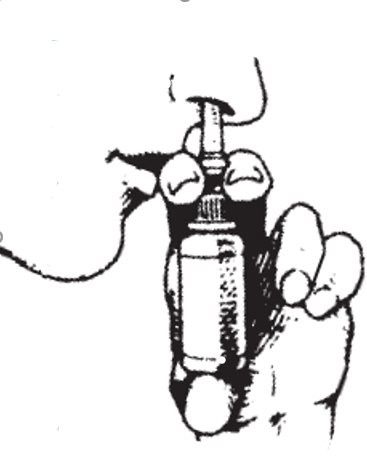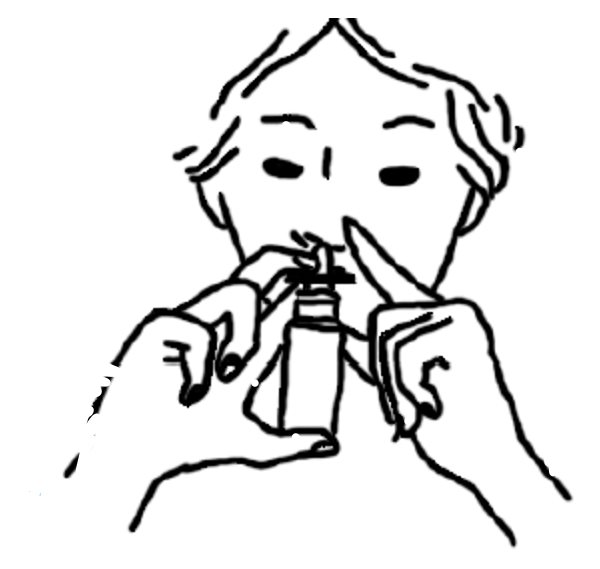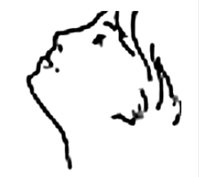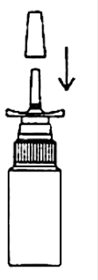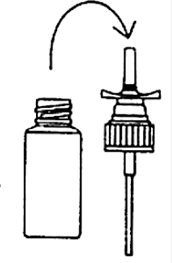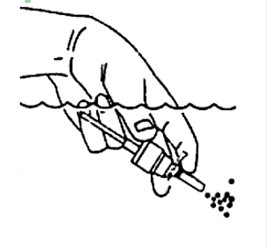 DRUG LABEL: Flunisolide
NDC: 68682-344 | Form: SOLUTION
Manufacturer: Oceanside Pharmaceuticals
Category: prescription | Type: HUMAN PRESCRIPTION DRUG LABEL
Date: 20250502

ACTIVE INGREDIENTS: FLUNISOLIDE 0.25 mg/1 mL
INACTIVE INGREDIENTS: BENZALKONIUM CHLORIDE 0.1 mg/1 mL; BUTYLATED HYDROXYANISOLE; CITRIC ACID MONOHYDRATE; EDETATE DISODIUM; HYDROCHLORIC ACID; POLYETHYLENE GLYCOL 3350; PROPYLENE GLYCOL; WATER; SODIUM CITRATE, UNSPECIFIED FORM; SODIUM HYDROXIDE

Flunisolide Nasal Solution USP, 0.025%

FOR INTRANASAL USE ONLY

DESCRIPTION

Flunisolide Nasal Solution USP, 0.025% is intended for administration as a spray to the nasal mucosa. Flunisolide, the active component of Flunisolide Nasal Solution, is an anti-inflammatory steroid.

Flunisolide is represented by the following structural formula:

C24H31FO6 Mol. Wt. 434.51

Chemical Name:

6α-fluoro-11β,16α,17,21-tetrahydroxypregna-1,4-diene-3,20-dione cyclic 16,17-acetal with acetone (USAN).

Flunisolide is a white to creamy white crystalline powder. It is soluble in acetone, sparingly soluble in chloroform, slightly soluble in methanol, and practically insoluble in water. It has a melting point of about 245°C.

After initial priming (5 to 6 sprays), each spray of the unit delivers a metered droplet spray of 100 mg formulation containing 25 mcg of flunisolide. The size of the droplets produced by the unit is in excess of 8 microns to facilitate deposition on the nasal mucosa. The contents of one nasal spray bottle delivers 200 sprays.

Each mL contains: ACTIVE: Flunisolide 0.25 mg (0.025%); INACTIVES: Butylated Hydroxyanisole, Citric Acid, Edetate Disodium Dihydrate, Polyethylene Glycol 3350, Propylene Glycol, Purified Water, and Sodium Citrate. Sodium Hydroxide and/or Hydrochloric Acid may be added to adjust pH (5.1–5.4). PRESERVATIVE: Benzalkonium Chloride 0.01%.

CLINICAL PHARMACOLOGY

Flunisolide has demonstrated potent glucocorticoid and weak mineralocorticoid activity in classical animal test systems. As a glucocorticoid, it is several hundred times more potent than the cortisol standard. Clinical studies with flunisolide have shown therapeutic activity on nasal mucous membranes with minimal evidence of systemic activity at the recommended doses.

A study in approximately 100 patients that compared the recommended dose of Flunisolide Nasal Solution with an oral dose providing equivalent systemic amounts of flunisolide has shown that the clinical effectiveness of Flunisolide Nasal Solution, when used topically as recommended, is due to its direct local effect and not to an indirect effect through systemic absorption.

Following administration of flunisolide to man, approximately half of the administered dose is recovered in the urine and half in the stool: 65 to 70% of the dose recovered in urine is the primary metabolite, which has undergone loss of the 6α fluorine and addition of a 6β hydroxy group. Flunisolide is well absorbed but is rapidly converted by the liver to the much less active primary metabolite and to glucuronate and/or sulfate conjugates. Because of first-pass liver metabolism, only 20% of the flunisolide reaches the systemic circulation when it is given orally whereas 50% of the flunisolide administered intranasally reaches the systemic circulation unmetabolized. The plasma half-life of flunisolide is 1 to 2 hours.

The effects of flunisolide on hypothalamic-pituitary-adrenal (HPA) axis function have been studied in adult volunteers. Flunisolide was administered intranasally as a spray in total doses over 7 times the recommended dose (2,200 mcg, equivalent to 88 sprays/day) in 2 subjects for 4 days, about 3 times the recommended dose (800 mcg, equivalent to 32 sprays/day) in 4 subjects for 4 days, and over twice the recommended dose (700 mcg, equivalent to 28 sprays/day) in 6 subjects for 10 days. Early morning plasma cortisol concentrations and 24-hour urinary 17-ketogenic steroids were measured daily. There was evidence of decreased endogenous cortisol production at all three doses.

In controlled studies, Flunisolide Nasal Solution was found to be effective in reducing symptoms of stuffy nose, runny nose and sneezing in most patients. These controlled clinical studies have been conducted in 488 adult patients at doses ranging from 8 to 16 sprays (200-400 mcg) per day and 127 pediatric patients at doses ranging from 6 to 8 sprays (150 to 200 mcg) per day for periods as long as 3 months. In 170 patients who had cortisol levels evaluated at baseline and after 3 months or more of flunisolide treatment, there was no unequivocal flunisolide-related depression of plasma cortisol levels.

Clinical studies have shown that improvement is usually apparent within a few days after starting Flunisolide Nasal Solution.

The mechanisms responsible for the anti-inflammatory action of corticosteroids and for the activity of the aerosolized drug on the nasal mucosa are unknown.

INDICATIONS AND USAGE

Flunisolide Nasal Solution is indicated for the treatment of the nasal symptoms of seasonal or perennial rhinitis. Flunisolide Nasal Solution should not be used in the presence of untreated localized infection involving nasal mucosa.

CONTRAINDICATIONS

Hypersensitivity to any of the ingredients.

WARNINGS

The replacement of a systemic corticosteroid with a topical corticoid can be accompanied by signs of adrenal insufficiency, and in addition some patients may experience symptoms of withdrawal, e.g., joint and/or muscular pain, lassitude and/or depression. Patients previously treated for prolonged periods with systemic corticosteroids and transferred to flunisolide should be carefully monitored to avoid acute adrenal insufficiency in response to stress.

When transferred to flunisolide, careful attention must be given to patients previously treated for prolonged periods with systemic corticosteroids. This is particularly important in those patients who have associated asthma or other clinical conditions, where too rapid a decrease in systemic corticosteroids may cause a severe exacerbation of their symptoms.

The use of flunisolide with alternate-day prednisone systemic treatment could increase the likelihood of HPA suppression compared to a therapeutic dose of either one alone. Therefore, flunisolide treatment should be used with caution in patients already on alternate-day prednisone regimens for any disease.

Persons who are on drugs that suppress the immune system are more susceptible to infections than healthy individuals. Chickenpox and measles, for example, can have a more serious or even fatal course in non-immune pediatric patients or adults on corticosteroids. In such pediatric patients or adults who have not had these diseases, particular care should be taken to avoid exposure. How the dose, route and duration of corticosteroid administration affects the risk of developing a disseminated infection is not known. The contribution of the underlying disease and/or prior corticosteroid treatment to the risk is also not known. If a nonimmune patient is exposed to chickenpox, prophylaxis with varicella zoster immune globulin (VZIG) may be indicated. If exposed to measles, prophylaxis with pooled intramuscular immunoglobulin (IG) may be indicated. (See the respective package insert for complete VZIG and IG prescribing information.) If chickenpox develops, treatment with antiviral agents may be considered.

PRECAUTIONS

General: Intranasal corticosteroids may also cause a reduction in growth velocity when administered to pediatric patients (see PRECAUTIONS, Pediatric Use).

Symptomatic relief may not occur in some patients for as long as 2 weeks. Although systemic effects are minimal at recommended doses, flunisolide should not be continued beyond 3 weeks in the absence of significant symptomatic improvement. In clinical studies with flunisolide administered intranasally, the development of localized infections of the nose and pharynx with Candida albicans has occurred only rarely. When such an infection develops, it may require treatment with appropriate local therapy or discontinuance of treatment with flunisolide.

Flunisolide is absorbed into the circulation. Use of excessive doses of flunisolide may suppress HPA function. Flunisolide should be used with caution, if at all, in patients with active or quiescent tuberculosis infection of the respiratory tract or in untreated fungal, bacterial or systemic viral infections or ocular herpes simplex.

Because of the inhibitory effect of corticosteroids on wound healing, in patients who have experienced recent nasal septal ulcers, recurrent epistaxis, nasal surgery or trauma, a nasal corticosteroid should be used with caution until healing has occurred.

Although systemic effects have been minimal with recommended doses, this potential increases with excessive dosages. Therefore, larger than recommended doses should be avoided.

Information for Patients: Patients should use flunisolide at regular intervals since its effectiveness depends on its regular use. The patient should take the medication as directed. It is not acutely effective and the prescribed dosage should not be increased. Instead, nasal vasoconstrictors or oral antihistamines may be needed until the effects of flunisolide are fully manifested. One to two weeks may pass before full relief is obtained. The patient should contact the physician if symptoms do not improve, or if the condition worsens, or if sneezing or nasal irritation occurs.

Persons who are on immunosuppressant doses of corticosteroids should be warned to avoid exposure to chickenpox or measles. Patients should also be advised that if they are exposed, medical advice should be sought without delay.

For the proper use of this unit and to attain maximum improvement, the patient should read and follow the accompanying Patient Instructions carefully.

Patients should be advised to clear their nasal passages of secretions prior to use.

Carcinogenesis, Mutagenesis, Impairment of Fertility: In mice, flunisolide at an oral dose of 500 mcg/kg/day (approximately 6 times the maximum recommended daily intranasal dose in adults and children on a mg/m^2 basis) for 21 months was negative for carcinogenic effects. In rats, administration of flunisolide at an oral dose of 2.5 mcg/kg/day (less than the maximum recommended daily intranasal dose in adults and children on a mg/m^2 basis) for 24 months resulted in an increased incidence of mammary gland adenoma and islet cell adenoma of the pancreas in females. There were no significant increases in the incidence of any tumor type in rats at an oral dose of 1 mcg/kg (less than the maximum recommended daily intranasal dose in adults and children on a mg/m^2 basis).

Flunisolide showed no mutagenic activity in in vitro test systems including the Ames Assay and the Rec-Assay, and no clastogenic activity in either the in vitro chromosomal aberration assay in Chinese hamster lung fibroblast cells or the in vivo mouse bone marrow chromosomal aberration assay.

Flunisolide, at an oral dose of 200 mcg/kg/day (approximately 4 times the maximum recommended daily intranasal dose in adults on a mg/m^2 basis) produced impaired fertility in female rats, but was devoid of such effect at oral doses less than or equal to 40 mcg/kg/day (approximately equal to the maximum recommended daily intranasal dose in adults on a mg/m^2 basis).

Pregnancy: As with other corticosteroids, flunisolide has been shown to be teratogenic and fetotoxic in rabbits and rats at oral doses of 40 and 200 mcg/kg/day, respectively (approximately 2 and 4 times, respectively, the maximum recommended daily intranasal dose in adults on a mg/m^2 basis). There are no adequate and well-controlled studies in pregnant women. Flunisolide should be used during pregnancy only if the potential benefit justifies the potential risk to the fetus.

Nursing Mothers: It is not known whether this drug is excreted in human milk. Because other corticosteroids are excreted in human milk, caution should be exercised when flunisolide is administered to nursing women.

Pediatric Use: Flunisolide Nasal Solution is not recommended for use in pediatric patients less than 6 years of age as safety and efficacy have not been assessed in this age group. Controlled clinical studies have shown that intranasal corticosteroids may cause a reduction in growth velocity in pediatric patients. This effect has been observed in the absence of laboratory evidence of HPA-axis suppression, suggesting that growth velocity is a more sensitive indicator of systemic corticosteroid exposure in pediatric patients than some commonly used tests of HPA-axis function. The long-term effects of this reduction in growth velocity associated with intranasal corticosteroids, including the impact on final adult height, are unknown. The potential for “catch up” growth following discontinuation of treatment with intranasal corticosteroids has not been adequately studied. The growth of pediatric patients receiving intranasal corticosteroids, including Flunisolide Nasal Solution, should be monitored routinely (e.g., via stadiometry). The potential growth effects of prolonged treatment should be weighed against clinical benefits obtained and the availability of safe and effective noncorticosteroid treatment alternatives. To minimize the systemic effects of intranasal corticosteroids, including Flunisolide Nasal Solution, each patient should be titrated to the lowest dose that effectively controls his/her symptoms.

Geriatric Use: Clinical studies of Flunisolide Nasal Solution did not include sufficient numbers of subjects aged 65 and older to determine whether they respond differently from younger subjects. Other reported clinical experience has not identified differences in responses between the elderly and younger patients. In general, dose reduction for an elderly patient should be cautious, usually starting at the low end of the dosing range, reflecting a greater frequency of decreased hepatic, renal, or cardiac function, and of concomitant disease or other drug therapy.

ADVERSE REACTIONS

Adverse reactions reported in controlled clinical trials and long-term open studies in 595 patients treated with Flunisolide Nasal Solution are described below. Of these patients, 409 were treated for 3 months or longer, 323 for 6 months or longer, 259 for 1 year or longer, and 91 for 2 years or longer.

In general, side effects elicited in the clinical studies have been primarily associated with the nasal mucous membranes. The most frequent complaints were those of mild transient nasal burning and stinging, which were reported in approximately 45% of the patients treated with Flunisolide Nasal Solution in placebo-controlled and long-term studies. These complaints do not usually interfere with treatment; in only 3% of patients was it necessary to decrease dosage or stop treatment because of these symptoms. Approximately the same incidence of mild transient nasal burning and stinging was reported in patients on placebo as was reported in patients treated with Flunisolide Nasal Solution in controlled studies, implying that these complaints may be related to the vehicle or the delivery system. The incidence of complaints of nasal burning and stinging decreased with increasing duration of treatment.

Other side effects reported at a frequency of 5% or less were: nasal congestion, sneezing, epistaxis and/or bloody mucous, nasal irritation, watery eyes, sore throat, nausea and/or vomiting, and headaches. As with other nasally inhaled corticosteroids, nasal septal perforations have been reported in rare instances with the use of Flunisolide Nasal Solutions. Temporary or permanent loss of the sense of smell and taste have also been reported with the use of Flunisolide Nasal Solutions.

Systemic corticosteroid side effects were not reported during the controlled clinical trials. If recommended doses are exceeded, or if individuals are particularly sensitive, symptoms of hypercorticism, i.e., Cushing’s syndrome, could occur. Cases of growth suppression have been reported for intranasal corticosteroids (including Flunisolide Nasal Solution) (see PRECAUTIONS, Pediatric Use).

To report SUSPECTED ADVERSE REACTIONS, contact Oceanside Pharmaceuticals at 1-800-321-4576 or FDA at 1-800-FDA-1088 or www.fda.gov/medwatch.

OVERDOSAGE

Flunisolide, infused intravenously, at doses up to 4 mg/kg in mice, rats and dogs (approximately 45,300 and 90 times, respectively, the maximum recommended daily intranasal dose in adults and children on a mg/m^2 basis) was without lethality.

DOSAGE AND ADMINISTRATION

Adults: The recommended starting dose of Flunisolide Nasal Solution is 2 sprays (50 mcg) in each nostril 2 times a day (total dose 200 mcg/day). If needed, this dose may be increased to 2 sprays in each nostril 3 times a day (total dose 300 mcg/day).

Pediatric Patients 6 to 14 years: The recommended starting dose of Flunisolide Nasal Solution is 1 spray (25 mcg) in each nostril 3 times a day or 2 sprays (50 mcg) in each nostril 2 times a day (total dose 150 to 200 mcg/day). Flunisolide Nasal Solution is not recommended for use in pediatric patients less than 6 years of age as safety and efficacy studies, including possible adverse effects on growth, have not been conducted.

Maximum total daily doses should not exceed 8 sprays in each nostril for adults (total dose 400 mcg/day) and 4 sprays in each nostril for pediatric patients under 14 years of age (total dose 200 mcg/day). Since there is no evidence that exceeding the maximum recommended dosage is more effective and increased systemic absorption would occur, higher doses should be avoided.

After the desired clinical effect is obtained, the maintenance dose should be reduced to the smallest amount necessary to control the symptoms. Approximately 15% of patients with perennial rhinitis may be maintained on as little as 1 spray in each nostril per day.

For priming and repriming the nasal spray unit after storage: The patient should remove the dust cover. Put two fingers on “shoulders” of pump unit, and place thumb on bottom of bottle. Push bottle with thumb FIRMLY and QUICKLY 5-6 times or until fine spray appears. Now your pump is primed. The patient must prime the pump unit again if it has not been used for 5 days or more, or if it has been disassembled for cleaning.

Directions for Use: A patient leaflet of instructions accompanies each package of Flunisolide Nasal Solution.

WARNING: Do not spray in eyes.

HOW SUPPLIED

Flunisolide Nasal Solution USP, 0.025% is supplied in a nasal pump dispenser with dust cover and with patient instructions in the following size:

NDC 68682-344-25 25 mL bottle

Each 25 mL Flunisolide Nasal Solution spray bottle contains 6.25 mg (0.25 mg/mL), 200 metered sprays of flunisolide.

Storage: Store between 15°C to 25ºC (59°F to 77°F) [see USP Controlled Room Temperature].

Keep out of reach of children

Distributed by:
Oceanside Pharmaceuticals, a division of

Bausch Health US, LLC

Bridgewater, NJ 08807 USA

Manufactured by:
Bausch Health Companies Inc.
Laval, Quebec H7L 4A8, Canada

© 2025 Bausch Health Companies Inc. or its affiliates

Revised: 05/2025

90006200

PATIENT INSTRUCTIONS

Flunisolide Nasal Solution USP, 0.025%

– HOW TO USE YOUR NASAL PUMP UNIT –

Your nasal spray unit with the pump requires no assembly.
Just follow the simple instructions below.

IMPORTANT INFORMATION ON FLUNISOLIDE NASAL SOLUTION:

1. You should use Flunisolide Nasal Solution at regular intervals since its effectiveness depends on its regular use (see below).
2. It may take 1-2 weeks before full relief is obtained.
3. You should contact your physician if symptoms do not improve, if the condition worsens, or if sneezing, nasal irritation, or bleeding occurs.
4. You should contact your physician if you know you have been exposed to chickenpox or measles.

TO PRIME:

1. Remove the dust cover. Put two fingers on “shoulders” of pump unit, and place thumb on bottom of bottle. Push bottle with thumb FIRMLY and QUICKLY 5-6 times or until a fine spray appears. Now your pump is primed.
You must prime the pump unit again if you have not used it for 5 days or more, or if you have disassembled it for cleaning.
2. If the solution is delivered in a stream of liquid, it may fail to provide maximum benefit and cause some discomfort. A fine mist can be produced only by a rapid and firm pumping action.
3. Once your pump is primed, it’s ready to use.
NOTE: Keep dust cover on the pump unit when not in use.

TO USE:

1. Gently blow nose to clear nostrils. If nose is blocked, use medicine your doctor has recommended to open nasal passages.

2. Remove the dust cover. Be sure the pump unit is primed.

3. Place the spray tip into one nostril (tip should not reach far into nose). Bend head forward so spray will aim toward the back of the nose.

4. Hold pump as shown, resting back of index finger against upper lip. BE CAREFUL THAT FINGERS DO NOT SLIP OFF THE PUMP AS YOU SPRAY.

5. Point the tip toward the BACK and OUTER SIDE of the nose. Close other nostril with finger. Pump the spray by pushing bottle with thumb FIRMLY and QUICKLY and sniff gently at the same time. Your doctor will tell you whether to pump once or twice in each nostril.

6. After spraying in nostril, remove unit from nose and bend head back for a few seconds to let spray spread over back of nose.

7. Repeat Steps 5 and 6 in other nostril. You may feel brief burning or stinging after using the spray.
8. Keep dust cover on the pump unit when not in use.

TO CLEAN:

1. If spray nozzle becomes clogged, DO NOT ATTEMPT TO CLEAR IT USING A POINTED OBJECT. Remove the pump unit from bottle.

2. Soak only the pump unit in warm water. Squirt several times while holding under water.

3. Make sure the pump unit is dry. Assemble as before with 5 or 6 sprays before use.

Storage: Store between 15°C to 25ºC (59°F to 77°F) [see USP Controlled Room Temperature].

Distributed by:

Oceanside Pharmaceuticals, a division of

Bausch Health US, LLC

Bridgewater, NJ 08807 USA

Manufactured by:

Bausch Health Companies Inc.

Laval, Quebec H7L 4A8, Canada

© 2025 Bausch Health Companies Inc. or its affiliates

Revised: 05/2025

90006200

Package/Label Display Panel

NDC 68682-344-25

Flunisolide
Nasal
Solution,
USP 0.025%

FOR INTRANASAL
USE ONLY

Each Spray Delivers
25 mcg Flunisolide

200 Metered Sprays

Rx only

25 mL

Oceanside

Pharmaceuticals

9006000
20005733A